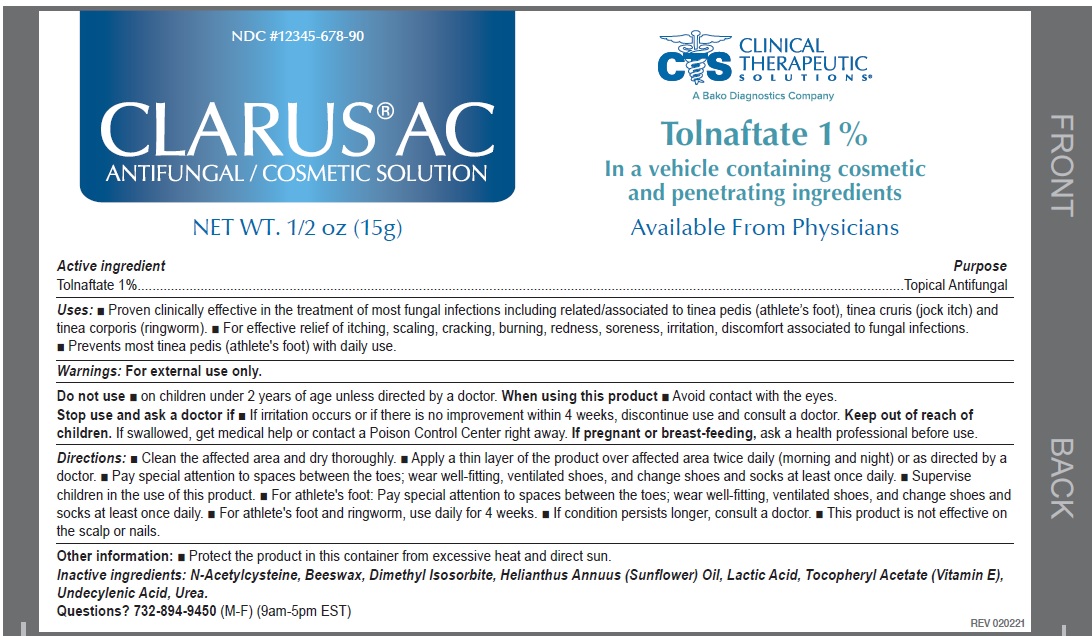 DRUG LABEL: CLARUS AC Antifungal Solution
NDC: 44577-128 | Form: LIQUID
Manufacturer: Clinical Therapeutic Solutions
Category: otc | Type: HUMAN OTC DRUG LABEL
Date: 20231110

ACTIVE INGREDIENTS: TOLNAFTATE 10 mg/1 g
INACTIVE INGREDIENTS: ACETYLCYSTEINE; YELLOW WAX; DIMETHYL ISOSORBIDE; HELIANTHUS ANNUUS FLOWERING TOP; LACTIC ACID; .ALPHA.-TOCOPHEROL ACETATE; UNDECYLENIC ACID; UREA

CLARUS AC Antifungal Solution

Active ingredient

Tolnaftate 1%

Purpose

Topical Antifungal

Uses:

- Proven clinically effective in the treatment of most fungal infections including related/associated to tinea pedis (athlete’s foot), tinea cruris (jock itch) and tinea corporis (ringworm).
- For effective relief of itching, scaling, cracking, burning, redness, soreness, irritation, discomfort associated to fungal infections.
- Prevents most tinea pedis (athlete's foot) with daily use.

Warnings:

For external use only.

Do not use

- on children under 2 years of age unless directed by a doctor.

When using this product

- Avoid contact with the eyes.

Stop use and ask a doctor if

If irritation occurs or if there is no improvement within 4 weeks, discontinue use and consult a doctor.

Keep out of reach of children.

If swallowed, get medical help or contact a Poison Control Center right away.

Directions:

- Clean the affected area and dry thoroughly.
- Apply a thin layer of the product over affected area twice daily (morning and night) or as directed by a doctor.
- Pay special attention to spaces between the toes; wear well-fitting, ventilated shoes, and change shoes and socks at least once daily.Supervise children in the use of this product.
- For athlete's foot: Pay special attention to spaces between the toes; wear well-fitting, ventilated shoes, and change shoes and socks at least once daily.
- For athlete's foot and ringworm, use daily for 4 weeks.
- If condition persists longer, consult a doctor.
- This product is not effective on the scalp or nails.

Other information:

- Protect the product in this container from excessive heat and direct sun.

Inactive ingredients:

N-Acetylcysteine, Beeswax, Dimethyl Isosorbite, Helianthus Annuus (Sunflower) Oil, Lactic Acid, Tocopheryl Acetate (Vitamin E), Undecylenic Acid, Urea.

Questions?

(M-F) (9am-5pm EST) 732-894-9450